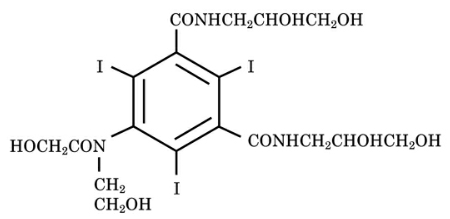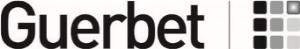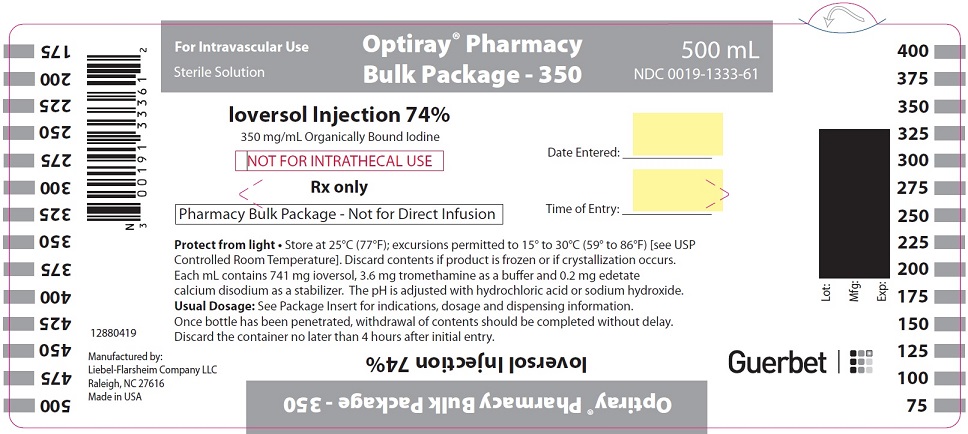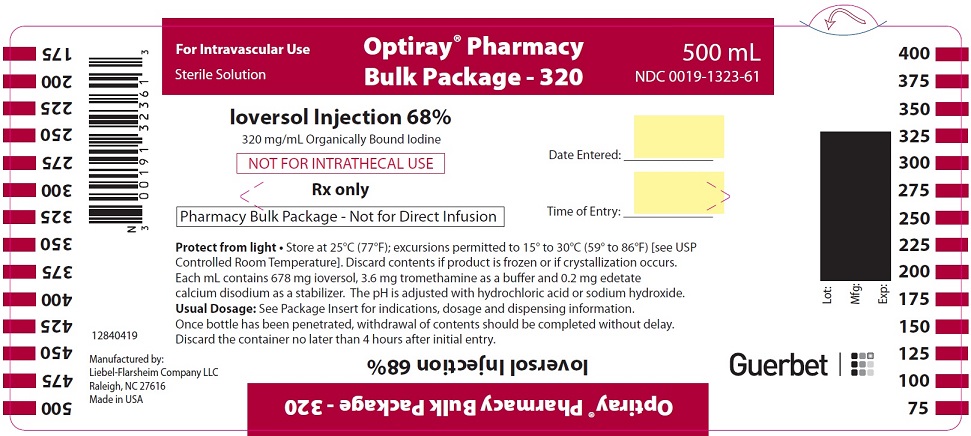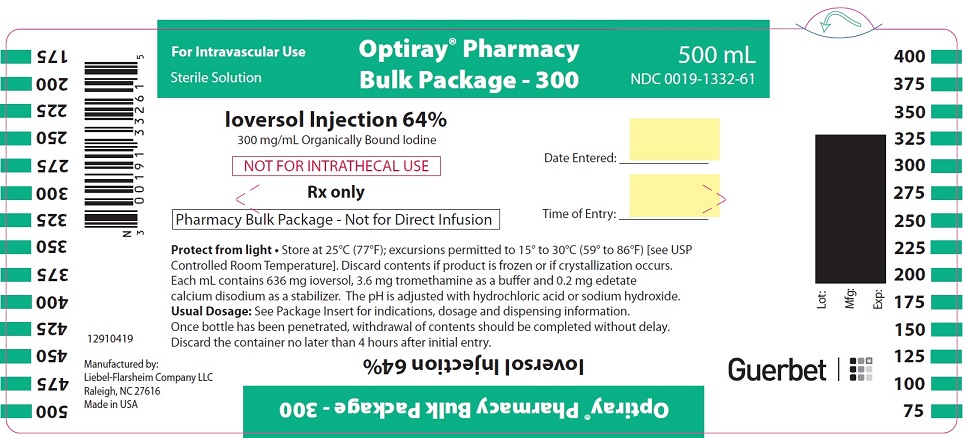 DRUG LABEL: Optiray

NDC: 0019-1333 | Form: INJECTION
Manufacturer: Liebel-Flarsheim Company LLC
Category: prescription | Type: HUMAN PRESCRIPTION DRUG LABEL
Date: 20251229

ACTIVE INGREDIENTS: IOVERSOL 741 mg/1 mL
INACTIVE INGREDIENTS: TROMETHAMINE 3.6 mg/1 mL; EDETATE CALCIUM DISODIUM 0.2 mg/1 mL; HYDROCHLORIC ACID; SODIUM HYDROXIDE

HIGHLIGHTS OF PRESCRIBING INFORMATION

These highlights do not include all the information needed to use OPTIRAY PHARMACY BULK PACKAGE safely and effectively. See full prescribing information for OPTIRAY.
OPTIRAY®(ioversol) Injection for intravenous use
Initial U.S. Approval: 1988

WARNING: NOT FOR INTRATHECAL USE

See full prescribing information for complete boxed warning.
Inadvertent intrathecal administration may cause death, convulsion, cerebral hemorrhage, coma, paralysis, arachnoiditis, acute renal failure, cardiac arrest, seizures, rhabdomyolysis, hyperthermia, and brain edema [see Warnings and Precautions (5.1)].

1 INDICATIONS AND USAGE

OPTIRAY is a radiographic contrast agent indicated for the following:
Intra-arterial Procedures (1.1)
Adults:

- Cerebral Arteriography (320 mg iodine/mL)
- Peripheral Arteriography (320, 350 mg iodine/mL)
- Visceral and Renal Arteriography, Aortography (320 mg iodine/mL)
- Coronary Arteriography and Left Ventriculography (320, 350 mg iodine/mL)

Pediatric Patients:Angiocardiography (320, 350 mg iodine/mL)

Intravenous Procedures (1.2)
Adults:

- Computed tomography (CT) Imaging of Head and Body (320, 350 mg iodine/mL)
- Venography (320, 350 mg iodine/mL)
- Intravenous Excretory Urography (320, 350 mg iodine/mL)
- Intravenous Digital Subtraction Angiography (350 mg iodine/mL)

Pediatric Patients:CT Imaging of the Head and Body, and Intravenous Excretory Urography (320mg iodine/mL).

2 DOSAGE AND ADMINISTRATION

The Pharmacy Bulk Package is not for direct infusion.

Adjust the volume and concentration of OPTIRAY. Modify the dose accounting for factors such as age, body weight, vessel size, blood flow rate within the vessel. Please see details in full Prescribing Information. (2)

3 DOSAGE FORMS AND STRENGTHS

OPTIRAY Pharmacy Bulk Package is available in two strengths:

Injection: 320 mg iodine/mL (ioversol 68%), 350 mg iodine/mL (ioversol 74%) in pharmacy bulk package bottles. (3)

4 CONTRAINDICATIONS

Symptomatic Hyperthyroidism (4)

5 WARNINGS AND PRECAUTIONS

- Hypersensitivity Reactions: life-threatening or fatal reactions can occur. Always have emergency equipment and trained personnel available. (5.2)
- Contrast Induced Acute Kidney Injury: Acute injury, including renal failure, can occur. Minimize dose and maintain adequate hydration to minimize risk. (5.3)
- Cardiovascular Adverse Reactions: hemodynamic disturbances including shock and cardiac arrest may occur during or after administration. (5.4)
- Thyroid Dysfunction in Pediatric Patients 0 to 3 Years of Age: Individualize thyroid function monitoring based on risk factors such as prematurity. (5.8)

6 ADVERSE REACTIONS

The most common reaction is nausea, occurring at a rate of greater than 1 percent. (6.1)

To report SUSPECTED ADVERSE REACTIONS, contact LIEBEL-FLARSHEIM COMPANY LLC at 855-266-5037 or FDA at 1-800-FDA-1088 or www.fda.gov/medwatch.

8 USE IN SPECIFIC POPULATIONS

- Lactation: A lactating woman may pump and discard breast milk for 8 hours after OPTIRAY administration. (8.2)

FULL PRESCRIBING INFORMATION

WARNING: NOT FOR INTRATHECAL USE

Inadvertent intrathecal administration may cause death, convulsions, cerebral hemorrhage, coma, paralysis, arachnoiditis, acute renal failure, cardiac arrest, seizures, rhabdomyolysis, hyperthermia, and brain edema [see Warnings and Precautions (5.1)].

1 INDICATIONS AND USAGE

OPTIRAY is indicated for:

1.1 Intra-arterial

In adults

- OPTIRAY 320:cerebral arteriography, peripheral arteriography, visceral and renal arteriography, aortography, coronary arteriography, and left ventriculography.
- OPTIRAY 350:peripheral arteriography, coronary arteriography, and left ventriculography.

In pediatric patients

- OPTIRAY 320 and OPTIRAY 350:angiocardiography.

1.2 Intra-venous

In adults

- OPTIRAY 320:CT imaging of the head and body, venography, and intravenous excretory urography.
- OPTIRAY 350:CT imaging of the head and body, venography, intravenous excretory urography, and intravenous digital subtraction angiography (IV-DSA).

In pediatric patients

- OPTIRAY 320:CT imaging of the head and body, and intravenous excretory urography.

2 DOSAGE AND ADMINISTRATION

2.1 Important Dosage and Administration Instructions

- OPTIRAY is for intravascular use only [see Boxed Warning, Contraindications (4), Warnings and Precautions (5.1)] .
- Use sterile technique for all handling and administration of OPTIRAY.
- Inspect glass container prior to use for breakage or other damage and do not use damaged containers.
- Warm OPTIRAY and administer at body or room temperature.
- Inspect OPTIRAY for particulate matter or discoloration before administration. Do not administer if OPTIRAY contains particulate matter or is discolored.
- Do not mix OPTIRAY with other drugs, solutions or total parenteral nutrition mixtures.
- Use the lowest dose necessary to obtain adequate visualization.
- Adjust the volume and concentration of OPTIRAY. Modify the dose accounting for factors such as age, body weight, vessel size, blood flow rate within the vessel, anticipated pathology, degree and extent of opacification required, structure(s) or area to be examined, disease processes affecting the patient, and equipment and technique to be employed.
- Avoid extravasation when injecting OPTIRAY; especially in patients with severe arterial or venous disease [see Warnings and Precautions (5.6)] .
- Hydrate patients before and after OPTIRAY administration [see Warnings and Precautions (5.3)].

Directions for Proper Use of OPTIRAY Pharmacy Bulk Package

- The Pharmacy Bulk Package is not for direct infusion.
- Penetrate the container closure only one time, utilizing a suitable sterile transfer device or dispensing set which allows measured distribution of the contents.
- Transfer OPTIRAY from the Pharmacy Bulk Package only in a suitable work area, such as a laminar flow hood, utilizing aseptic technique.
- Withdraw container contents immediately. However, should this not be possible, a maximum time of 4 hours from initial closure entry is permitted to complete fluid transfer operations.
- Temperature of container after the closure has been entered should not exceed 25°C (77°F).

2.2 Intra-arterial Procedures in Adults

- Cerebral Arteriography

Use OPTIRAY 320. The recommended dose for visualization of cerebral arteries is shown below (may repeat as necessary):

Diagnostic area | Dose | Maximum Cumulative Dose
carotid or vertebral arteries | 2 to 12 mL | 200 mL
aortic arch injection; (four vessel study) | 20 to 50 mL | 200 mL

- Peripheral Arteriography

Use OPTIRAY 320 or OPTIRAY 350. The recommended dose for visualization of peripheral arteries is shown below (may repeat as necessary):

Diagnostic area | Dose | Maximum Cumulative Dose
aorta-iliac runoff | 60 mL (range 20 to 90 mL) | 250 mL
common iliac, femoral | 40 mL (range 10 to 50 mL) | 250 mL
subclavian, brachial | 20 mL (range 15 to 30 mL) | 250 mL

- Visceral and Renal Arteriography and Aortography

Use OPTIRAY 320. The recommended dose for visualization for the aorta and visceral arteries is shown below (may repeat as necessary):

Diagnostic area | Dose | Maximum Cumulative Dose
aorta | 45 mL (range 10 to 80 mL) | 250 mL
celiac | 45 mL (range 12 to 60 mL) | 250 mL
superior mesenteric | 45 mL (range 15 to 60 mL) | 250 mL
renal or inferior mesenteric | 9 mL (range 6 to 15 mL) | 250 mL

- Coronary Arteriography and Left Ventriculography

Use OPTIRAY 320 or OPTIRAY 350. The recommended dose for visualization of the coronary arteries and left ventricle is shown below (may repeat as necessary):

Diagnostic area | Dose | Maximum Cumulative Dose
left coronary | 8 mL (range 2 to 10 mL) | 250 mL
right coronary | 6 mL (range 1 to 10 mL) | 250 mL
left ventricle | 40 mL (range 30 to 50 mL) | 250 mL

2.3 Intravenous Procedures in Adults

- Computed Tomography

Use OPTIRAY 320 or OPTIRAY 350 for head and body imaging.

Head Imaging
The recommended dosing is shown below:

- Scan immediately after completion of the intravenous administration.

 | Infusion
OPTIRAY 320 | 50 to 150 mL
OPTIRAY 350 | 50 to 150 mL

Body Imaging
OPTIRAY may be administered by bolus injection, by rapid infusion, or by a combination of both. The recommended dosing is shown below:

- Scanning interval will vary with indication and target organ

 | Bolus Injection | Infusion
OPTIRAY 320 | 25 to 75mL | 50 to 150 mL
OPTIRAY 350 | 25 to 75mL | 50 to 150 mL

- Venography

Use OPTIRAY 320 or OPTIRAY 350. The recommended dose is 50 to 100 mL per extremity; with a maximum cumulative dose of 250 mL.

- Intravenous Urography

Use OPTIRAY 350 or OPTIRAY 320. The recommended dose is shown below:

 | Usual Dose | High Dose Urography | Maximum Dose
OPTIRAY 320 | 50 to 75mL | 1.5 to 2 mL/kg | 150 mL
OPTIRAY 350 | 50 to 75mL | 1.4 mL/kg | 150 mL

- Intravenous Digital Subtraction Angiography (IV-DSA)

Use OPTIRAY 350. The recommended dose range per injection is 30 to 50 mL; may repeat as necessary with a maximum cumulative dose of 250mL.

Injection rates will vary depending on the site of catheter placement and vessel size.

- Central catheter injections are usually made at a rate of between 10 and 30 mL/second.
- Peripheral injections are usually made at a rate of between 12 and 20 mL/second.

2.4 Pediatric Dosing

Intra-arterial Procedures

- Angiocardiography

Use OPTIRAY 350 or OPTIRAY 320. The recommended single ventricular dose is 1.25 mL/kg (range 1 mL/kg to 1.5 mL/kg). The maximum cumulative dose is 5 mL/kg up to a maximum total volume of 250 mL.

Intravenous Procedures

- Computed Tomography

Use OPTIRAY 320.

Head and Body Imaging
The recommended dose in pediatric patients is 1.5 mL/kg to 2 mL/kg (range 1 mL/kg to 3 mL/kg).

- Intravenous Urography

Use OPTIRAY 320. The recommended dose for pediatric patients is 1 mL/kg to 1.5 mL/kg (range 0.5 mL/kg to 3 mL/kg); with a maximum cumulative dose not exceeding 3 mL/kg.

3 DOSAGE FORMS AND STRENGTHS

Injection: clear, colorless to pale yellow solutions containing no undissolved solids, available in the following strengths and multiple-dose containers:

Imaging Product | mg of ioversol per mL | mg of organically bound iodine per mL | Pharmacy Bulk Pack Presentation
OPTIRAY 320 (Ioversol 68%) | 678 | 320 | Yes
OPTIRAY 350 (Ioversol 74%) | 741 | 350 | Yes

4 CONTRAINDICATIONS

Symptomatic hyperthyroidism.

5 WARNINGS AND PRECAUTIONS

5.1 Risks Associated with Inadvertent Intrathecal Administration

OPTIRAY is indicated for intravascular use only [see Dosage and Administration (2.1)] . Inadvertent intrathecal administration can cause death, convulsions, cerebral hemorrhage, coma, paralysis, arachnoiditis, acute renal failure, cardiac arrest, seizures, rhabdomyolysis, hyperthermia, and brain edema.

5.2 Hypersensitivity Reactions

OPTIRAY can cause life-threatening or fatal hypersensitivity reactions including anaphylaxis and anaphylactic shock. Manifestations include respiratory arrest, laryngospasm, bronchospasm, angioedema, and shock. Most severe reactions develop shortly after the start of the injection (e.g. within 1 to 3 minutes), but delayed reactions may occur. There is an increased risk in patients with a history of a previous reaction to contrast agent, and known allergies (i.e., bronchial asthma, drug, or food allergies), and other hypersensitivities. Premedication with antihistamines or corticosteroids to avoid or minimize possible allergic reactions does not prevent serious life-threatening reactions, but may reduce both their incidence and severity.

Obtain a history of allergy, hypersensitivity, or prior hypersensitivity reactions to iodinated contrast agents. Always have emergency resuscitation equipment and trained personnel available and monitor all patients for hypersensitivity reactions.

5.3 Contrast Induced Acute Kidney Injury

Acute kidney injury, including renal failure, may occur after OPTIRAY administration. Risk factors include: pre-existing renal impairment, dehydration, diabetes mellitus, congestive heart failure, advanced vascular disease, elderly age, concomitant use of nephrotoxic or diuretic medications, multiple myeloma / paraproteinaceous diseases, repetitive and/or large doses of an iodinated contrast agent.

Use the lowest necessary dose of OPTIRAY in patients with renal impairment. Adequately hydrate patients prior to and following OPTIRAY administration. Do not use laxatives, diuretics, or preparatory dehydration prior to OPTIRAY administration.

5.4 Cardiovascular Adverse Reactions

OPTIRAY increases the circulatory osmotic load and may induce acute or delayed hemodynamic disturbances in patients with congestive heart failure, severely impaired renal function, combined renal and hepatic disease, combined renal and cardiac disease, particularly when repetitive or large doses are administered.

Life-threatening or fatal cardiovascular reactions have occurred with the use of OPTIRAY, including cardiac arrest, hypotensive collapse, and shock. Most deaths occur within 10 minutes of injection; with cardiovascular disease as the main underlying factor. Cardiac decompensation, serious arrhythmias, and myocardial ischemia or infarction can occur during coronary arteriography and ventriculography.

Based upon literature reports, deaths from the administration of iodinated contrast agents range from 6.6 per 1 million (0.00066 percent) to 1 in 10,000 patients (0.01 percent). Use the lowest necessary dose of OPTIRAY in patients with congestive heart failure and always have emergency resuscitation equipment and trained personnel available. Monitor all patients for severe cardiovascular reactions.

5.5 Thromboembolic Events

Angiocardiography
Serious, fatal, thromboembolic events causing myocardial infarction and stroke can occur during angiographic procedures with OPTIRAY. During these procedures, increased thrombosis and activation of the complement system occurs. Risk factors for thromboembolic events include: length of procedure, catheter and syringe material, underlying disease state, and concomitant medications.

To minimize thromboembolic events use meticulous angiographic technique. Avoid blood remaining in contact with syringes containing OPTIRAY, which increases the risk of clotting. Avoid angiocardiography in patients with homocystinuria because of the risk of inducing thrombosis and embolism [see Clinical Pharmacology (12.2)] .

5.6 Extravasation and Injection Site Reactions

Extravasation can occur with OPTIRAY administration, particularly in patients with severe arterial or venous disease and can be associated with pain, hemorrhage and necrosis. Ensure intravascular placement of catheters prior to injection. Monitor patients for extravasation and advise patients to seek medical care for progression of symptoms.

5.7 Thyroid Storm in Patients with Hyperthyroidism

OPTIRAY is contraindicated in patients with symptomatic hyperthyroidism [see Contraindications (4)] . Thyroid storm has occurred following the intravascular use of iodinated radiopaque agents in patients with hyperthyroidism or with an autonomously functioning thyroid nodule. Evaluate the risk in such patients before use of OPTIRAY.

5.8 Thyroid Dysfunction in Pediatric Patients 0 to 3 Years of Age

Thyroid dysfunction characterized by hypothyroidism or transient thyroid suppression has been reported after both single exposure and multiple exposures to iodinated contrast media (ICM) in pediatric patients 0 to 3 years of age.

Younger age, very low birth weight, prematurity, underlying medical conditions affecting thyroid function, admission to neonatal or pediatric intensive care units, and congenital cardiac conditions are associated with an increased risk of hypothyroidism after ICM exposure. Pediatric patients with congenital cardiac conditions may be at the greatest risk given that they often require high doses of contrast during invasive cardiac procedures.

An underactive thyroid during early life may be harmful for cognitive and neurological development and may require thyroid hormone replacement therapy. After exposure to ICM, individualize thyroid function monitoring based on underlying risk factors, especially in term and preterm neonates.

5.9 Hypertensive Crisis in Patients with Pheochromocytoma

Hypertensive crisis has occurred after the use of iodinated radiopaque contrast agents in patient with pheochromocytoma. Closely monitor patients when administering OPTIRAY if pheochromocytoma or catecholamine-secreting paraganglioma is suspected. Inject the minimum amount of OPTIRAY necessary and have measures for treatment of hypertensive crisis readily available.

5.10 Sickle Cell Crisis in Patients with Sickle Cell Disease

Iodinated contrast agents may promote sickling in individuals who are homozygous for sickle cell disease. Hydrate patients prior to and following OPTIRAY administration, use OPTIRAY only if the necessary imaging information cannot be obtained with alternative imaging modalities, and inject the minimum amount necessary.

5.11 Severe Cutaneous Adverse Reactions

Severe cutaneous adverse reactions (SCAR) may develop from 1 hour to several weeks after intravascular contrast agent administration. These reactions include Stevens-Johnson syndrome and toxic epidermal necrolysis (SJS/TEN), acute generalized exanthematous pustulosis (AGEP) and drug reaction with eosinophilia and systemic symptoms (DRESS). Reaction severity may increase and time to onset may decrease with repeat administration of a contrast agent; prophylactic medications may not prevent or mitigate severe cutaneous adverse reactions. Avoid administering OPTIRAY to patients with a history of a severe cutaneous adverse reaction to OPTIRAY.

6 ADVERSE REACTIONS

The following clinically significant adverse reactions are described elsewhere in the labeling:

- Risks Associated with Inadvertent Intrathecal Administration [see Warnings and Precautions (5.1)]
- Hypersensitivity Reactions [see Warnings and Precautions (5.2)]
- Contrast Induced Acute Kidney Injury [see Warnings and Precautions (5.3)]
- Cardiovascular Adverse Reactions [see Warnings and Precautions (5.4)]
- Thromboembolic Events [see Warnings and Precautions (5.5)]
- Thyroid Dysfunction in Pediatric Patients 0 to 3 Years of Age [see Warnings and Precautions (5.8)]
- Severe Cutaneous Adverse Reactions [see Warnings and Precautions (5.10)

6.1 Clinical Studies Experience

Adult Patients
Because clinical trials are conducted under widely varying conditions, adverse reaction rates observed in the clinical trials of a drug cannot be directly compared to rates in the clinical trials of another drug and may not reflect the rates observed in practice.

The following table shows reactions based upon clinical trials with OPTIRAY (ioversol) in 4,187 patients. Adverse reactions are listed by organ system according to clinical importance. More severe reactions are listed before others in a system regardless of incidence. The most common reaction is nausea, occurring at a rate of 1 percent.

Cardiac disorders
Cardiac arrest, myocardial infarction, arrhythmia, atrioventricular block complete, atrioventricular block, nodal rhythm, bradycardia, angina pectoris, palpitations

Ear and labyrinth disorders
Vertigo, tinnitus

Eye disorders
Vision blurred, periorbital edema, conjunctivitis

Gastrointestinal disorders
Vomiting, abdominal pain, dysphagia, dry mouth

General disorders and administration site conditions
Chest pain, pain, injection site pain, injection site hematoma, extravasation, pyrexia, swelling, asthenia, malaise, fatigue, chills

Infections and infestations
Rhinitis

Injury, poisoning, and procedural complications
Heart injury, vascular pseudoaneurysm

Investigations
Electrocardiogram ST segment depression, blood pressure decreased

Metabolism and nutrition disorders
Acidosis

Musculoskeletal and connective tissue disorders
Muscular weakness, muscle spasms, back pain

Nervous system disorders
Cerebral infarction, aphasia, tremor, dizziness, presyncope, headache, paraesthesia, dysgeusia

Psychiatric disorders
Hallucination, visual hallucination, disorientation, anxiety

Renal and urinary disorders
Urinary retention, renal pain, polyuria

Respiratory, thoracic, and mediastinal disorders
Laryngeal edema, hypoxia, pulmonary edema, dyspnea, hyperventilation, cough, sneezing,
nasal congestion

Skin and subcutaneous tissue disorders
Urticaria, rash, pruritus, swelling face, hyperhidrosis, erythema

Vascular disorders
Hypertension, hypotension, arterial spasm, vasospasm, vasodilation, flushing

Pediatric Patients
In clinical trials involving 311 patients for pediatric angiocardiography, contrast enhanced computed tomographic imaging of the head and body, and intravenous excretory urography; 6% of patients reported an adverse reactions, with the most common adverse reactions being nausea and fever. Adverse reactions reported were similar in quality and frequency to the adverse events reported by adults.

6.2 Postmarketing Experience

The following adverse drug reactions have been reported during post-approval use of OPTIRAY. Because these reactions are reported voluntarily from a population of uncertain size, it is not always possible to reliably estimate frequency or establish a casual relationship to drug exposure.

Cardiac disorders:coronary artery spasm, cyanosis, arrhythmia (ventricular fibrillation, tachycardia, extrasystole), ECG abnormal.

Endocrine disorders: Hyperthyroidism, hypothyroidism.

Eye disorders:temporary blindness, conjunctivitis (including eye irritation, ocular hyperemia, watery eyes).

Gastrointestinal disorders:tongue edema, salivary hypersecretion.

General disorders and administration site conditions:injection site reactions including pain, hemorrhage, and necrosis especially after extravasation [see Warnings and Precautions (5.6)] , face edema, feeling hot.

Immune system disorders:hypersensitivity reactions including fatal anaphylactic shock.

Nervous system disorders:seizure, loss of consciousness, somnolence, hypoesthesia, dyskinesia, amnesia.

Respiratory disorders:respiratory arrest, asthma, bronchospasm, laryngeal spasm and obstruction, throat irritation, dysphonia.

Skin and subcutaneous tissue disorders:Reactions range from mild (e.g. rash, erythema, pruritus, urticaria, and skin discoloration) to severe: [e.g. Stevens-Johnson syndrome and toxic epidermal necrolysis (SJS/TEN)], acute generalized exanthematous pustulosis (AGEP) and drug reaction with eosinophilia and systemic symptoms (DRESS).

Vascular Disorders:phlebitis, thrombosis.

7 DRUG INTERACTIONS

7.1 Drug-Drug Interactions

Metformin

In patients with renal impairment, metformin can cause lactic acidosis. Iodinated contrast agents appear to increase the risk of metformin induced lactic acidosis, possibly as a result of worsening renal function. Stop metformin at the time of, or prior to, OPTIRAY administration in patients with an eGFR between 30 and 60 mL/min/1.73 m2; in patients with a history of hepatic impairment, alcoholism or heart failure; or in patients who will be administered intra-arterial iodinated contrast agents. Re-evaluate eGFR 48 hours after the imaging procedure, and reinstitute only after renal function is stable.

Radioactive Iodine

Administration of iodinated contrast agents may interfere with thyroid uptake of radioactive iodine (I 131) and decrease therapeutic efficacy in patients with carcinoma of the thyroid. The decrease in efficacy lasts for 6-8 weeks.

Oral Cholecystographic Contrast Agents

Renal toxicity has been reported in patients with liver impairment who were given oral cholecystographic agents followed by intravascular contrast agents. Administration of OPTIRAY should be postponed in patients who have recently received a cholecystographic contrast agent.

7.2 Drug/Laboratory Test Interactions

Protein-Bound Iodine, Radioactive Iodine Determinations

The results of protein bound iodine and radioactive iodine uptake studies, which depend on iodine estimation, will not accurately reflect thyroid function for up to 16 days following administration of iodinated contrast agent. However, thyroid function tests that do not depend on iodine estimations, e.g., T3 resin uptake and total or free thyroxine (T4) assays are not affected.

8 USE IN SPECIFIC POPULATIONS

8.1 Pregnancy

Risk Summary
Postmarketing data with OPTIRAY use in pregnant women are insufficient to determine if there is a risk of drug-associated adverse developmental outcomes. Ioversol crosses the placenta and reaches fetal tissues in small amounts [see Data]. In animal reproduction studies, no adverse developmental effects were observed following daily intravenous administrations of ioversol to pregnant rats (from Gestation Day 7 to 17) and rabbits (Gestation Day 6 to 18) at doses 0.35 and 0.71 times, respectively, the maximum recommended human dose.

The estimated background risk of major birth defects and miscarriage for the indicated population is unknown. All pregnancies have a background risk of major birth defects, loss, or other adverse outcomes. In the U.S. general population, the estimated background risk of major birth defects and miscarriages in clinically recognized pregnancies is 2-4% and 15-20%, respectively.

Data

Human Data
Literature reports show that ioversol crosses the placenta and is visualized in the digestive tract of exposed infants after birth.

Animal Data
Developmental toxicity studies were conducted with ioversol given intravenously at doses of 0, 0.2, 0.8, and 3.2 g iodine/kg/day from Gestation Day7 to 17 and 6 to 18, in rats and rabbits, respectively. No adverse effects on embryo-fetal development were observed in either species at the maximum dose tested (3.2 g iodine/kg/day). Maternal toxicity was observed in rabbits at 0.8 and 3.2 g iodine/kg/day.

8.2 Lactation

Risk Summary
There is no information about the presence of ioversol in human or animal milk, the effects of the drug on the breastfed infant, or the effects of the drug on milk production. However, iodinated contrast agents are excreted unchanged in human milk in very low amounts with poor absorption from the gastrointestinal tract of the breastfed infant. The developmental and health benefits of breastfeeding should be considered along with the mother’s clinical need for OPTIRAY and any potential adverse effects on the breastfed infant from OPTIRAY or from the underlying maternal condition.

Clinical Considerations
Interruption of breastfeeding after exposure to iodinated contrast agents is not necessary because the potential exposure of the breastfed infant to iodine is small. However, a lactating woman may consider interrupting breastfeeding and pumping and discarding breast milk for 8 hours (approximately 5 elimination half-lives) after OPTIRAY administration in order to minimize drug exposure to a breast fed infant.

8.4 Pediatric Use

Safety and effectiveness in pediatric patients have been established for the use of OPTIRAY 350 and OPTIRAY 320 in angiocardiography; and for OPTIRAY 320 in contrast enhanced computed tomographic imaging of the head and body, and intravenous excretory urography. Use of OPTIRAY 350 and OPTIRAY 320 in these age groups is based on controlled clinical trials involving 159 patients for pediatric angiocardiography; contrast enhanced computed tomographic imaging of the head and body, and intravenous excretory urography. In general, the types of adverse reactions reported are similar to those of adults [see Adverse Reactions (6.1)] .

Safety and effectiveness of OPTIRAY 350 and OPTIRAY 320 have not been established in pediatric patients less than 1 month of age.

Pediatric patients at higher risk of experiencing adverse reactions to OPTIRAY include patients with: asthma, sensitivity to medication and/or allergens, congestive heart failure, serum creatinine greater than 1.5 mg/dL, or age less than 12 months. Thyroid function tests indicative of hypothyroidism or transient thyroid suppression have been uncommonly reported following iodinated contrast media administration in pediatric patients, including infants. Some patients were treated for hypothyroidism [See Adverse Reactions (6.2)] .

Thyroid function tests indicative of thyroid dysfunction, characterized by hypothyroidism or transient thyroid suppression have been uncommonly reported following iodinated contrast media administration in pediatric patients, including term and preterm neonates;some patients were treated for hypothyroidism. After exposure to iodinated contrast media, individualize thyroid function monitoring in pediatric patients 0 to 3 years of age based on underlying risk factors, especially in term and preterm neonates [see Warnings and Precautions (5.8) and Adverse Reactions (6.2)].

8.5 Geriatric Use

OPTIRAY is substantially excreted by the kidney, and the risk of adverse reactions to OPTIRAY may be greater in patients with impaired renal function. Because elderly patients are more likely to have decreased renal function, dose selection should be cautious usually starting at the low end of the dosing range, reflecting the greater frequency of decreased hepatic, renal or cardiac function, and of concomitant disease or other drug therapy.

8.6 Renal Impairment

In patients with impaired renal function, the elimination half-life is prolonged. Ioversol can be removed by dialysis.

10 OVERDOSAGE

The adverse effects of overdosage are life-threatening and affect mainly the pulmonary and cardiovascular system. Treatment of an overdosage is directed toward the support of all vital functions and prompt institution of symptomatic therapy.

Ioversol does not bind to plasma or serum protein and is, therefore, dialyzable.

11 DESCRIPTION

11.1 Chemical Characteristics

OPTIRAY (ioversol injection) is a non-ionic radiographic contrast agent. OPTIRAY formulations are sterile, nonpyrogenic, aqueous solutions intended for intravascular use. Each bottle is to be used as a Pharmacy Bulk Package for dispensing multiple single dose preparations utilizing a suitable transfer device. Ioversol is designated chemically as N,N'-Bis (2,3-dihydroxypropyl)-5-[ N-(2-hydroxyethyl) -glycolamido] -2,4,6-triiodoisophthalamide. The molecular weight of ioversol is 807.11 and the organically bound iodine content is 47.2%.
The structural formula of ioversol is as follows:

OPTIRAY Pharmacy Bulk Package is available in two strengths:

- OPTIRAY 320(ioversol injection 68%): Each mL contains 320 mg organically bound iodine, 678 mg of ioversol, 3.6 mg tromethamine, 0.2 mg edetate calcium disodium.

- OPTIRAY 350(ioversol injection 74%): Each mL contains 350 mg organically bound iodine, 741 mg ioversol, 3.6 mg tromethamine, 0.2 mg edetate calcium disodium.

The pH of the OPTIRAY formulations has been adjusted to 6.0 to 7.4 with hydrochloric acid or sodium hydroxide. All solutions are sterilized by autoclaving and contain no preservatives. Ioversol does not dissociate in solution.

11.2 Physical Characteristics

Some physical and chemical properties of these formulations are listed below:

 | OPTIRAY 320 | OPTIRAY 350
Ioversol content (mg/mL) | 678 | 741
Iodine content (mg l/mL) | 320 | 350
Osmolality (mOsm/kg water) | 702 | 792
Viscosity (cps)
at 25°C | 9.9 | 14.3
at 37°C | 5.8 | 9.0
Specific Gravity at 37°C | 1.371 | 1.405

The OPTIRAY formulations are clear, colorless to pale yellow solutions containing no undissolved solids. Crystallization does not occur at room temperature. OPTIRAY solutions have osmolalities 2.3 to 2.8 times that of plasma (285 mOsm/kg water) as shown in the above table and are hypertonic under conditions of use.

12 CLINICAL PHARMACOLOGY

12.1 Mechanism of Action

Intravascular injection of ioversol opacifies those vessels in the path of the flow of the contrast medium, permitting radiographic visualization of the internal structures until significant hemodilution occurs.

Ioversol may be visualized in the renal parenchyma within 30 to 60 seconds following rapid intravenous injection. Opacification of the calyces and pelves in patients with normal renal function becomes apparent within 1 to 3 minutes, with optimum contrast occurring within 5 to 15 minutes.

OPTIRAY enhances computed tomographic imaging through augmentation of radiographic efficiency. The degree of density enhancement is directly related to the iodine content in an administered dose; peak iodine blood levels occur immediately following rapid intravenous injection. Blood levels fall rapidly within 5 to 10 minutes and the vascular compartment half-life is approximately 20 minutes. This can be accounted for by the dilution in the vascular and extravascular fluid compartments which causes an initial sharp fall in plasma concentration. Equilibration with the extracellular compartments is reached in about 10 minutes; thereafter, the fall becomes exponential.

12.2 Pharmacodynamics

Following administration of OPTIRAY, the degree of enhancement is directly related to the iodine content in an administered dose. Peak iodine plasma levels occur immediately following rapid injection. The time to maximum contrast enhancement can vary, depending on the organ, from the time that peak blood iodine concentrations are reached to one hour after intravenous bolus administration. When a delay between peak blood iodine concentrations and peak contrast is present, it suggests that radiographic contrast enhancement is at least in part dependent on the accumulation of iodine-containing medium within the lesion and outside the blood pool.
For angiography, contrast enhancement is greatest immediately (15 seconds to 120 seconds) after rapid injection. Iodinated contrast agents may be visualized in the renal parenchyma within 30-60 seconds following rapid intravenous injection. Opacification of the calyces and pelves in patients with normal renal function becomes apparent within 1-3 minutes, with optimum contrast occurring within 5-15 minutes.

12.3 Pharmacokinetics

Based on the blood clearance curves for 12 healthy volunteers (6 receiving 50 mL and 6 receiving 150 mL of OPTIRAY 320), the biological half-life was 1.5 hours for both doses.

Distribution
In an in vitrohuman plasma study, ioversol did not bind to protein. The volume of distribution in adults was 0.26 L/kg body weight, consistent with distribution to the extracellular space.

Elimination
Metabolism
Ioversol does not undergo significant metabolism, deiodination or biotransformation.

Excretion
Greater than 95% of the administered dose was excreted in urine within the first 24 hours, with the peak urine concentration occurring in the first two hours after administration.

13 NONCLINICAL TOXICOLOGY

13.1 Carcinogenesis, Mutagenesis, Impairment of Fertility

No long term animal studies have been performed to evaluate carcinogenic potential. Nonclinical studies show that this drug is not mutagenic and does not affect fertility.

13.2 Animal Toxicology and/or Pharmacology

Animal studies indicate that ioversol does not cross the blood-brain barrier.

16 HOW SUPPLIED/STORAGE AND HANDLING

16.1 How Supplied

OPTIRAY is a clear, colorless to pale yellow, sterile, pyrogen-free, aqueous solution available in two strengths. The products are supplied in containers from which the air has been displaced by nitrogen. OPTIRAY is supplied in the following configurations:

NDC Number

OPTIRAY Pharmacy Bulk Package - 350

6x500 mL Pharmacy Bulk Packages 0019-1333-61

OPTIRAY Pharmacy Bulk Package - 320

6x500 mL Pharmacy Bulk Packages 0019-1323-61

16.2 Storage

- Store at 25°C (77°F); excursions permitted to 15° to 30°C (59° to 86°F).
- Protect from strong daylight or direct exposure to the sun.
- Discard OPTIRAY containers, and their contents, if they are frozen or if crystallization occurs.

17 PATIENT COUNSELING INFORMATION

Hypersensitivity Reactions
Advise the patient concerning the risk of hypersensitivity reactions that can occur both during and after OPTIRAY administration. Advise the patient to report any signs or symptoms of hypersensitivity reactions during the procedure and to seek medical attention for signs or symptoms experienced after discharge [see Warnings and Precautions (5.2)] .

Advise patients to inform their physician if they develop a rash after receiving OPTIRAY [see Warnings and Precautions (5.11)] .

Contrast Induced Acute Kidney Injury
Advise the patient concerning appropriate hydration to decrease the risk of contrast induced kidney injury [see Warnings and Precautions (5.3)] .

Extravasation
If extravasation occurs during injection, advise patients to seek medical care for progression of symptoms [see Warnings and Precautions (5.6)] .

Thyroid Dysfunction
Advise parents/caregivers about the risk of developing thyroid dysfunction after OPTIRAY administration. Advise parents/caregivers about when to seek medical care for their child to monitor for thyroid function [see Warnings and Precautions (5.8)].

Manufactured by:
Liebel-Flarsheim Company LLC
Raleigh, NC 27616

Made in USA

GBT 13PB825

PACKAGE LABEL - PRINCIPAL DISPLAY PANEL - Optiray 350 PBP, 500 mL bottle label

For Intravascular Use
Sterile Solution
Optiray™ Pharmacy Bulk Package - 350
500 mL
NDC 0019-1333-61
IOVERSOL INJECTION 74%
350 mg/mL Organically Bound Iodine
NOT FOR INTRATHECAL USE
Rx only
Pharmacy Bulk Package - Not for Direct Infusion
Protect from light •Store at 25°C (77°F); excursions permitted to 15° to 30°C (59° to 86°F) [see USP Controlled Room Temperature]. Discard contents if product is frozen or if crystallization occurs. Each mL contains 741 mg ioversol, 3.6 mg tromethamine as a buffer and 0.2 mg edetate calcium disodium as a stabilizer. The pH is adjusted with hydrochloric acid or sodium hydroxide.
Usual Dosage:See Package Insert for indications, dosage and dispensing information. Once bottle has been penetrated, withdrawal of contents should be completed without delay. Discard the container no later than 4 hours after initial entry.
12880419

Manufactured by:
Liebel-Flarsheim Company LLC
Raleigh, NC 27616
Made in USA

PACKAGE LABEL - PRINCIPAL DISPLAY PANEL - Optiray 320 PBP, 500 mL bottle label

For Intravascular Use
Sterile Solution
Optiray™ Pharmacy Bulk Package - 320
500 mL
NDC 0019-1323-61 IOVERSOL INJECTION 68%
320 mg/mL Organically Bound Iodine
NOT FOR INTRATHECAL USE
Rx only
Pharmacy Bulk Package - Not for Direct Infusion
Protect from light •Store at 25°C (77°F); excursions permitted to 15° to 30°C (59° to 86°F) [see USP Controlled Room Temperature]. Discard contents if product is frozen or if crystallization occurs. Each mL contains 678 mg ioversol, 3.6 mg tromethamine as a buffer and 0.2 mg edetate calcium disodium as a stabilizer. The pH is adjusted with hydrochloric acid or sodium hydroxide.
Usual Dosage:See Package Insert for indications, dosage and dispensing information. Once bottle has been penetrated, withdrawal of contents should be completed without delay. Discard the container no later than 4 hours after initial entry.
12840419

Manufactured by:
Liebel-Flarsheim Company LLC
Raleigh, NC 27616
Made in USA

PACKAGE LABEL - PRINCIPAL DISPLAY PANEL - Optiray 300 PBP, 500 mL bottle label

For Intravascular Use
Sterile Solution
Optiray™ Pharmacy Bulk Package - 300
500 mL
NDC 0019-1332-61
IOVERSOL INJECTION 64%
300 mg/mL Organically Bound Iodine
NOT FOR INTRATHECAL USE
Rx only
Pharmacy Bulk Package - Not for Direct Infusion
Protect from light •Store at 25°C (77°F); excursions permitted to 15° to 30°C (59° to 86°F) [see USP Controlled Room Temperature]. Discard contents if product is frozen or if crystallization occurs. Each mL contains 636 mg ioversol, 3.6 mg tromethamine as a buffer and 0.2 mg edetate calcium disodium as a stabilizer. The pH is adjusted with hydrochloric acid or sodium hydroxide.
Usual Dosage:See Package Insert for indications, dosage and dispensing information. Once bottle has been penetrated, withdrawal of contents should be completed without delay. Discard the container no later than 4 hours after initial entry.
12910419
Manufactured by:
Liebel-Flarsheim Company LLC
Raleigh, NC 27616
Made in USA